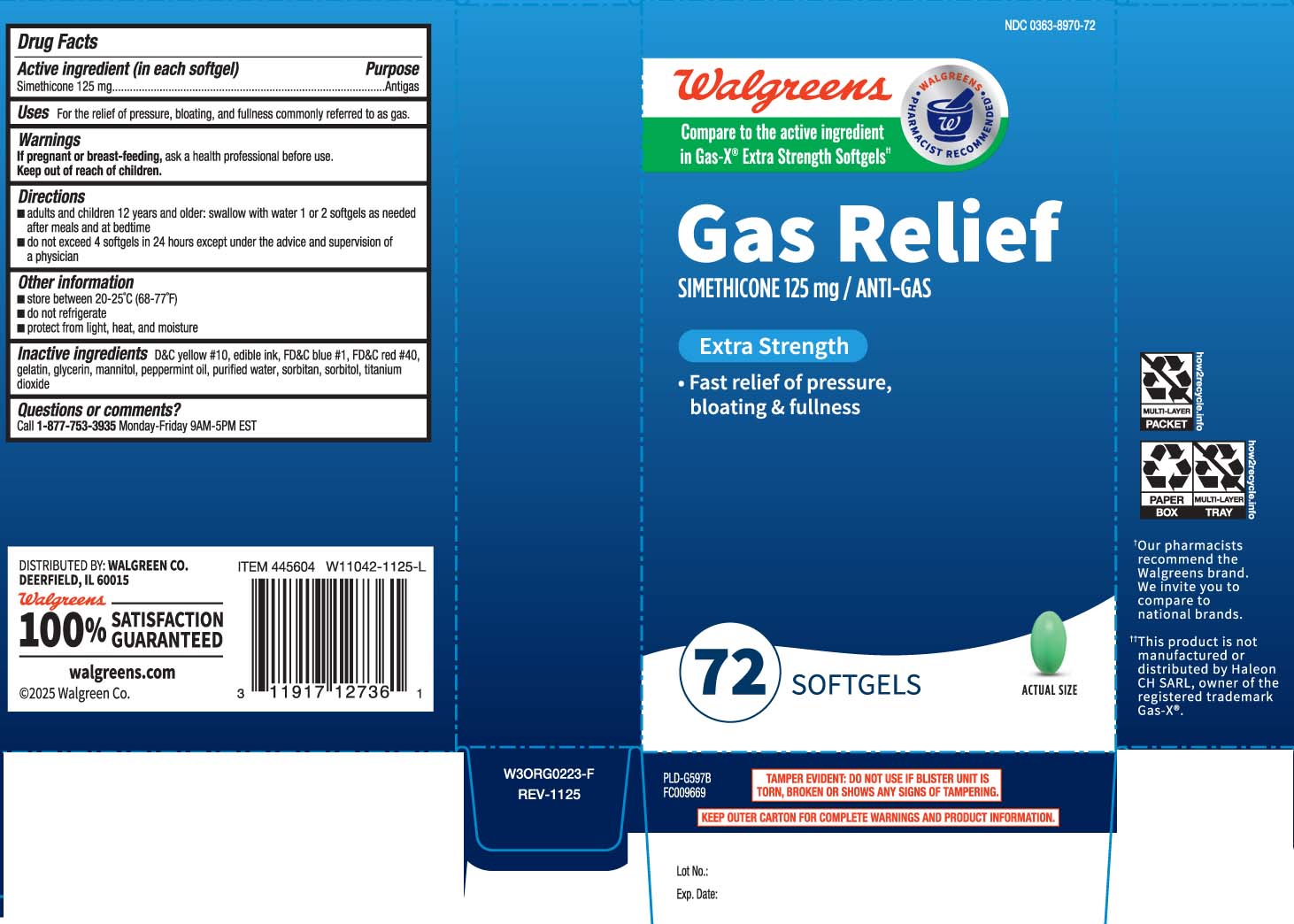 DRUG LABEL: Gas Relief
NDC: 0363-8970 | Form: CAPSULE, LIQUID FILLED
Manufacturer: Walgreens
Category: otc | Type: HUMAN OTC DRUG LABEL
Date: 20251125

ACTIVE INGREDIENTS: DIMETHICONE 125 mg/1 1
INACTIVE INGREDIENTS: D&C YELLOW NO. 10; FD&C BLUE NO. 1; FD&C RED NO. 40; GELATIN; GLYCERIN; PEPPERMINT OIL; WATER; SORBITAN; SORBITOL; TITANIUM DIOXIDE; MANNITOL

Drug Facts

Active ingredient (in each softgel)

Simethicone 125 mg

Purpose

Antigas

Uses

for the relief of pressure, bloating, and fullness commonly referred to as gas

Warnings

If pregnant or breast-feeding,

ask a health professional before use.

Directions

- adults and children 12 years and older: swallow with water 1 or 2 softgels as needed after meals and at bedtime
- do not exceed 4 softgels in 24 hours except under the advice and supervision of a physician

Other information

- store between 20-25°C (68-77°F)
- do not refrigerate
- protect from light, heat, and moisture

Inactive ingredients

D&C yellow #10, edible ink, FD&C blue #1, FD&C red #40, gelatin, glycerin, mannitol, peppermint oil, purified water, sorbitan, sorbitol, titanium dioxide

Questions or comments?

Call 1-877-753-3935 Monday-Friday 9AM-5PM EST

Principal Display Panel

Compare to the active ingredient in Gas-X® Extra Strength Softgels††

Gas Relief

SIMETHICONE 125 mg / ANTI-GAS

Extra Strength

- Fast relief of pressure, bloating & fullness

SOFTGELS

TAMPER EVIDENT: DO NOT USE IF BLISTER UNIT IS TORN, BROKEN OR SHOWS ANY SIGNS OF TAMPERING.

KEEP OUTER CARTON FOR COMPLETE WARNINGS AND PRODUCT INFORMATION.

††This product is not manufactured or distributed by Haleon CH SARL, owner of the registered trademark Gas- X®.

DISTRIBUTED BY: WALGREEN CO.

DEERFIELD, IL 60015

Product Label

WALGREENS Extra Strength Gas Relief